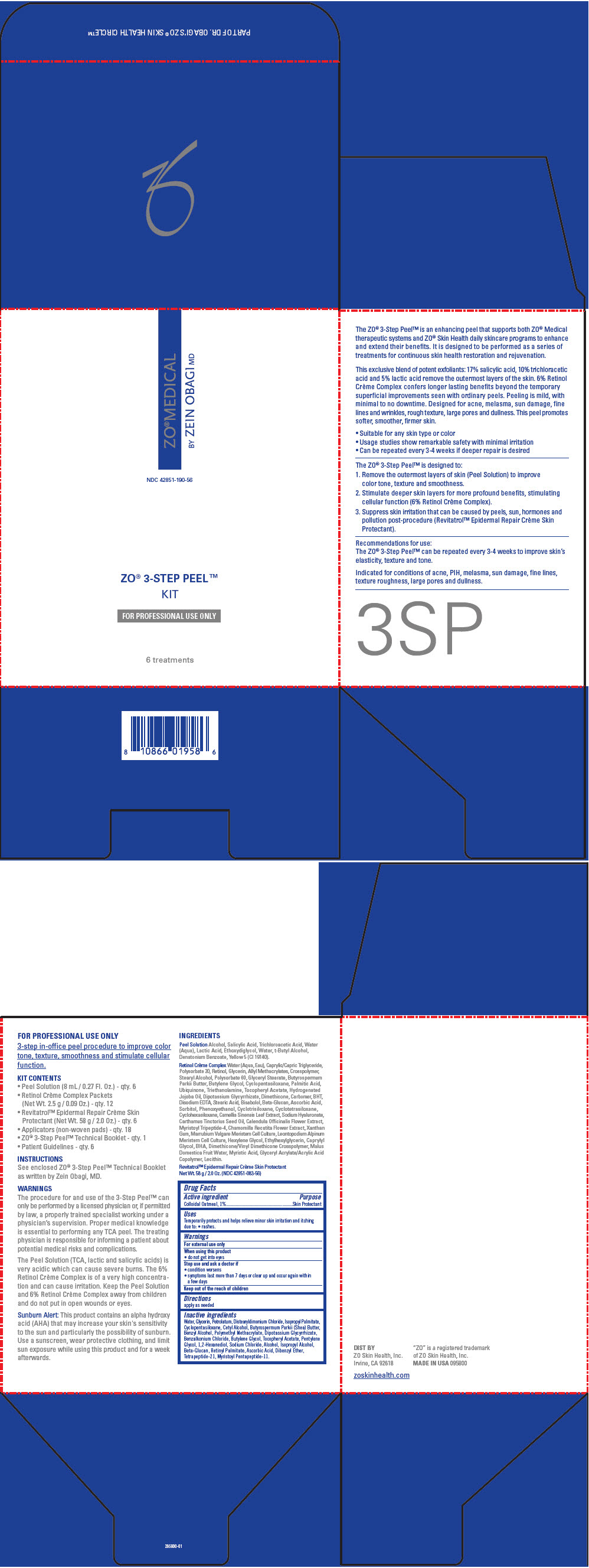 DRUG LABEL: ZO MEDICAL 3-STEP PEEL Kit
NDC: 42851-190 | Form: KIT | Route: TOPICAL
Manufacturer: ZO Skin Health, Inc.
Category: otc | Type: HUMAN OTC DRUG LABEL
Date: 20180403

ACTIVE INGREDIENTS: OATMEAL 10 mg/1 mL
INACTIVE INGREDIENTS: Water; Glycerin; Petrolatum; Distearyldimonium Chloride; Isopropyl Palmitate; CYCLOMETHICONE 5; Cetyl Alcohol; SHEA BUTTER; Benzyl Alcohol; POLY(METHYL METHACRYLATE; 450000 MW); GLYCYRRHIZINATE DIPOTASSIUM; Benzalkonium Chloride; Butylene Glycol; .ALPHA.-TOCOPHEROL ACETATE; Pentylene Glycol; 1,2-Hexanediol; Sodium Chloride; Alcohol; Isopropyl Alcohol; VITAMIN A PALMITATE; Ascorbic Acid; Dibenzyl Ether; Tetrapeptide-21

ZO® MEDICAL 3-STEP PEEL™ Kit

Drug Facts

Active ingredient

Colloidal Oatmeal, 1%

Purpose

Skin Protectant

Uses

Temporarily protects and helps relieve minor skin irritation and itching due to:

- rashes.

Warnings

For external use only

When using this product

- do not get into eyes

Stop use and ask a doctor if

- condition worsens
- symptoms last more than 7 days or clear up and occur again within a few days

Keep out of the reach of children

Directions

apply as needed

Inactive ingredients

Water, Glycerin, Petrolatum, Distearyldimonium Chloride, Isopropyl Palmitate, Cyclopentasiloxane, Cetyl Alcohol, Butyrospermum Parkii (Shea) Butter, Benzyl Alcohol, Polymethyl Methacrylate, Dipotassium Glycyrrhizate, Benzalkonium Chloride, Butylene Glycol, Tocopheryl Acetate, Pentylene Glycol, 1,2-Hexanediol, Sodium Chloride, Alcohol, Isopropyl Alcohol, Beta-Glucan, Retinyl Palmitate, Ascorbic Acid, Dibenzyl Ether, Tetrapeptide-21, Myristoyl Pentapeptide-11.

DIST BY
ZO Skin Health, Inc.
Irvine, CA 92618

PRINCIPAL DISPLAY PANEL - Kit Carton

ZO®MEDICAL

BY ZEIN OBAGI MD

NDC 42851-190-56

ZO® 3-STEP PEEL™
KIT

FOR PROFESSIONAL USE ONLY

6 treatments